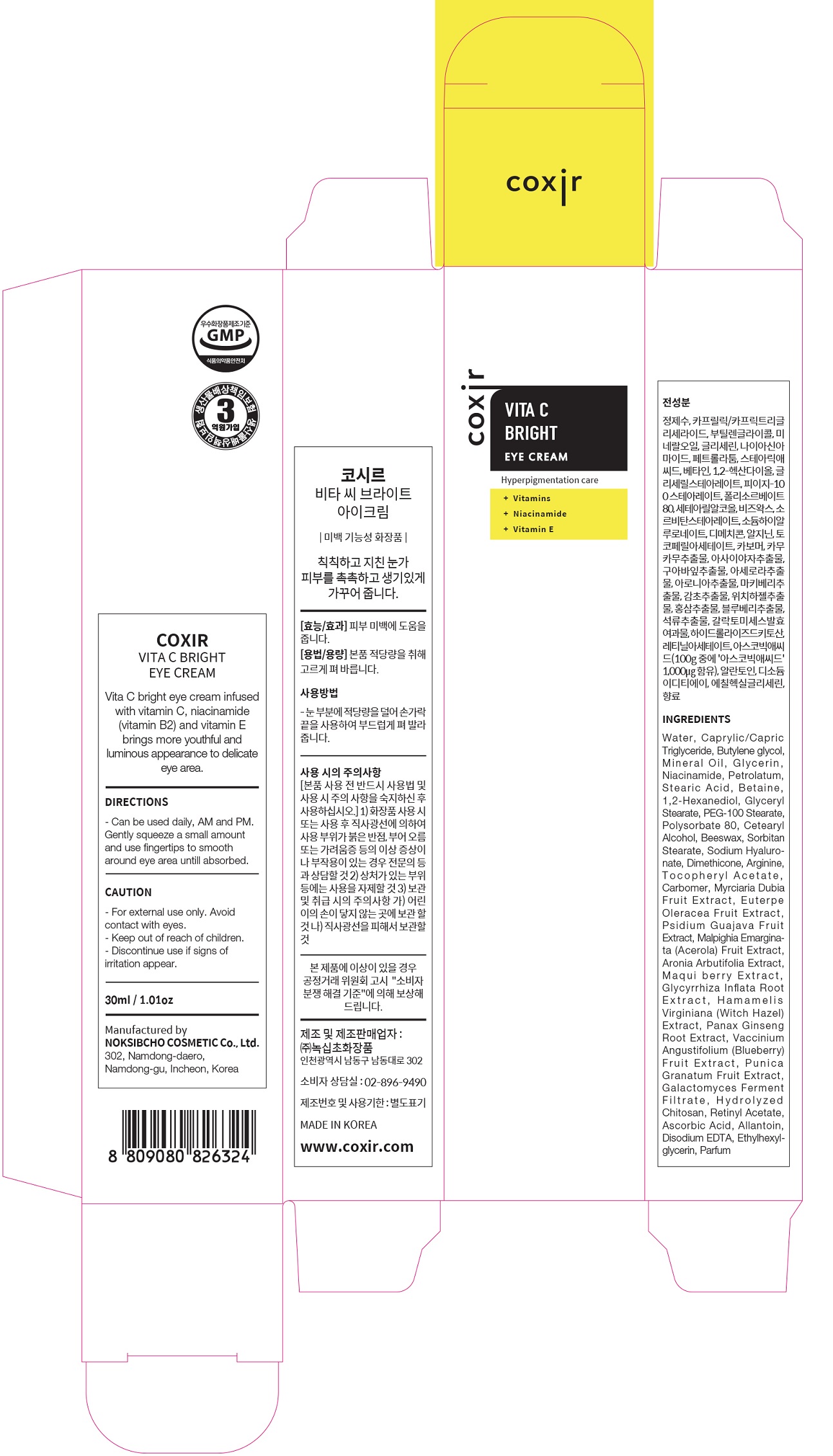 DRUG LABEL: Vita C Bright EyeCream
NDC: 73590-0016 | Form: CREAM
Manufacturer: NOKSIBCHO cosmetic Co., Ltd.
Category: otc | Type: HUMAN OTC DRUG LABEL
Date: 20200314

ACTIVE INGREDIENTS: NIACINAMIDE 2 g/100 mL
INACTIVE INGREDIENTS: WATER; BUTYLENE GLYCOL

Drug Facts

ACTIVE INGREDIENT

niacinamide, vitamins, vitamin E

INACTIVE INGREDIENT

Caprylic/Capric Triglyceride
Butylene glycol
Mineral Oil
Glycerin
Niacinamide
Petrolatum
Stearic Acid
Betaine
1,2-Hexanediol
Glyceryl Stearate
PEG-100 Stearate
Polysorbate 80
Cetearyl Alcohol
Glyceryl Stearate
Beeswax
Sorbitan Stearate
Sodium Hyaluronate
Dimethicone
Arginine
Tocopheryl Acetate
Carbomer
Myrciaria Dubia Fruit Extract
Euterpe Oleracea Fruit Extract
Psidium Guajava Fruit Extract
Malpighia Emarginata (Acerola) Fruit Extract
Aronia Arbutifolia Extract
Maqui berry Extract
Glycyrrhiza Inflata Root Extract
Hamamelis Virginiana (Witch Hazel) Extract
Panax Ginseng Root Extract
Vaccinium Angustifolium (Blueberry) Fruit Extract
Punica Granatum Fruit Extract
Galactomyces Ferment Filtrate
Hydrolyzed Chitosan
Retinyl Acetate
Ascorbic Acid
Allantoin
Disodium EDTA
Ethylhexylglycerin
Parfum
Ethylhexylglycerin
Parfum

PURPOSE

hyperpigmentation care

keep out of reach of the children

INDICATIONS AND USAGE

apply proper amount and gently massage

WARNINGS

For external use only
When using this product

■ if the following symptoms occurs after use, stop use and consult with a skin specialist

red specks, swelling, itching

■ don’t use on the part where there is injury, eczema, or dermatitis

Keep out of reach of children

■ if swallowed, get medical help or contact a person control center immediately

DOSAGE AND ADMINISTRATION

for external use only